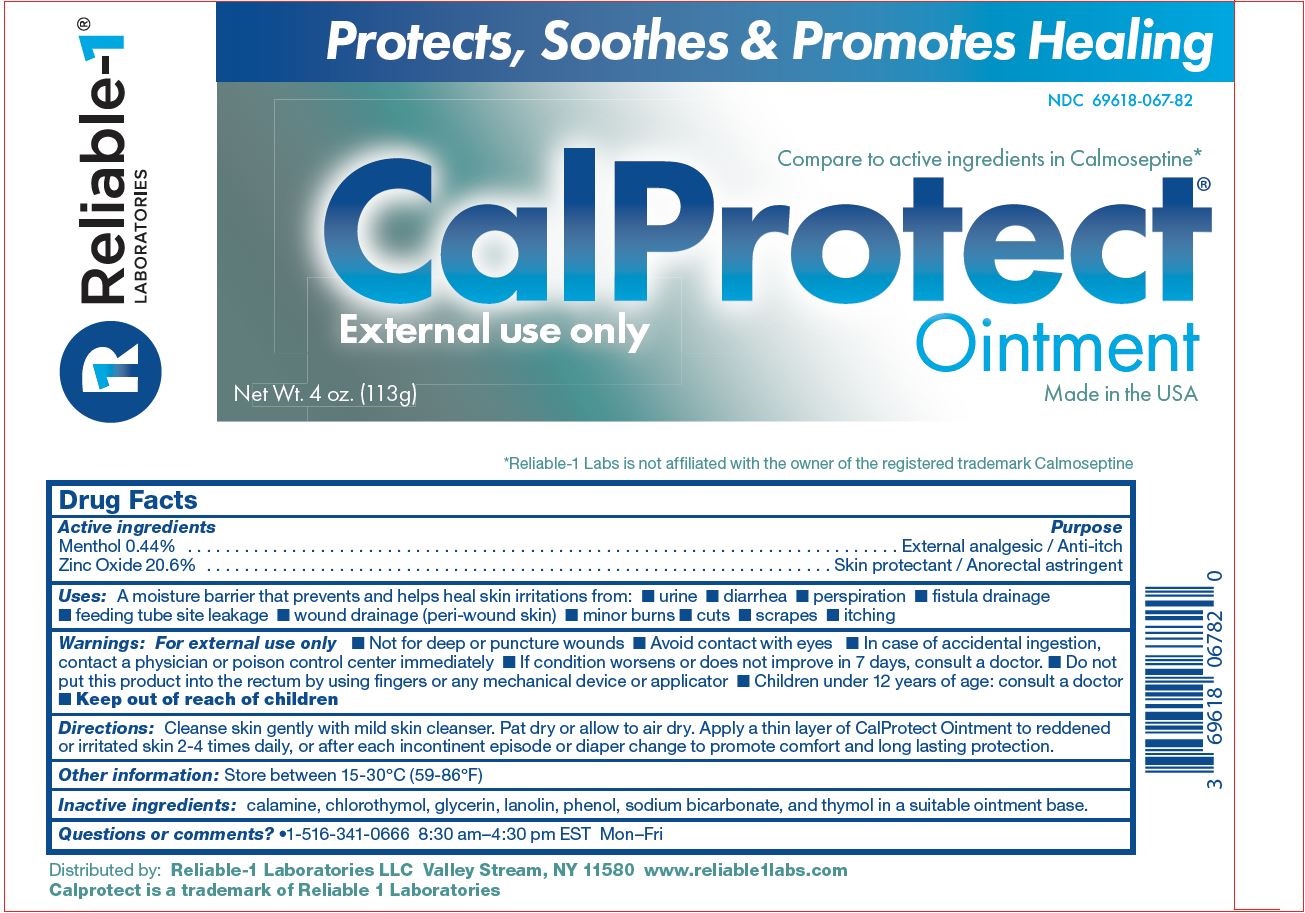 DRUG LABEL: Calprotect
NDC: 69618-067 | Form: OINTMENT
Manufacturer: Reliable 1 Laboratories LLC
Category: otc | Type: HUMAN OTC DRUG LABEL
Date: 20260219

ACTIVE INGREDIENTS: ZINC OXIDE 20.6 g/100 g; MENTHOL 0.44 g/100 g
INACTIVE INGREDIENTS: PHENOL; FERRIC OXIDE RED; CHLOROTHYMOL; GLYCERIN; THYMOL; LANOLIN; SODIUM BICARBONATE

Calprotect Ointment

Active ingredients

Menthol 0.44%

Zinc Oxide 20.6%

Purpose

External analgesic / Anti-itch

Skin protectant / Anorectal astrigent

Uses

A moisture barrier that prevents and helps heal skin irritations from

- urine
- diarrhea
- perspiration
- fistula drainage
- feeding tube site leakage
- wound drainage (per-wound skin)
- minor burns
- cuts
- scrapes
- itching

Warnings

For external use only

- Not for deep or puncture wounds
- Avoid contact with eyes
- Incase of accidental ingestion, contact a physician or posion contril immediately
- If condition worsens or does not improve in 7 days, consult a doctor
- Do not put this product into the rectum by using fingers or any machanical device or applicator
- Children under 12 years of age: consult a doctor

Keep out of reach of children

Directions

Cleanse skin gently with mild skin cleanser. Pat dry or allow to air dry. Apply a thin layer of Calprotect Ointment to reddened or irritated skin 2-4 times daily, or after each incontinent episode or diaper change to promote comfort and long lasting protection.

Other information

Store between 15-30°C (59-86°F)

Inactive ingredients

calamine, chlorothymol, glycerin, lanolin, phenol, sodium bicarbonate, and thymol in a suitable ointment base

Questions or comments?

1-516-341-0666 8:30 am-4:30 pm EST Mon-Fri

PACKAGE LABEL

Protects, Soothes & Promotes Healing

NDC 69618-067-82

Compare to active ingredients in Calmoseptine*

CalProtect Ointment

External use only

Made in the USA

*Reliable-1 Labs is not affiliated with the owner of the registered trademark Calmoseptine